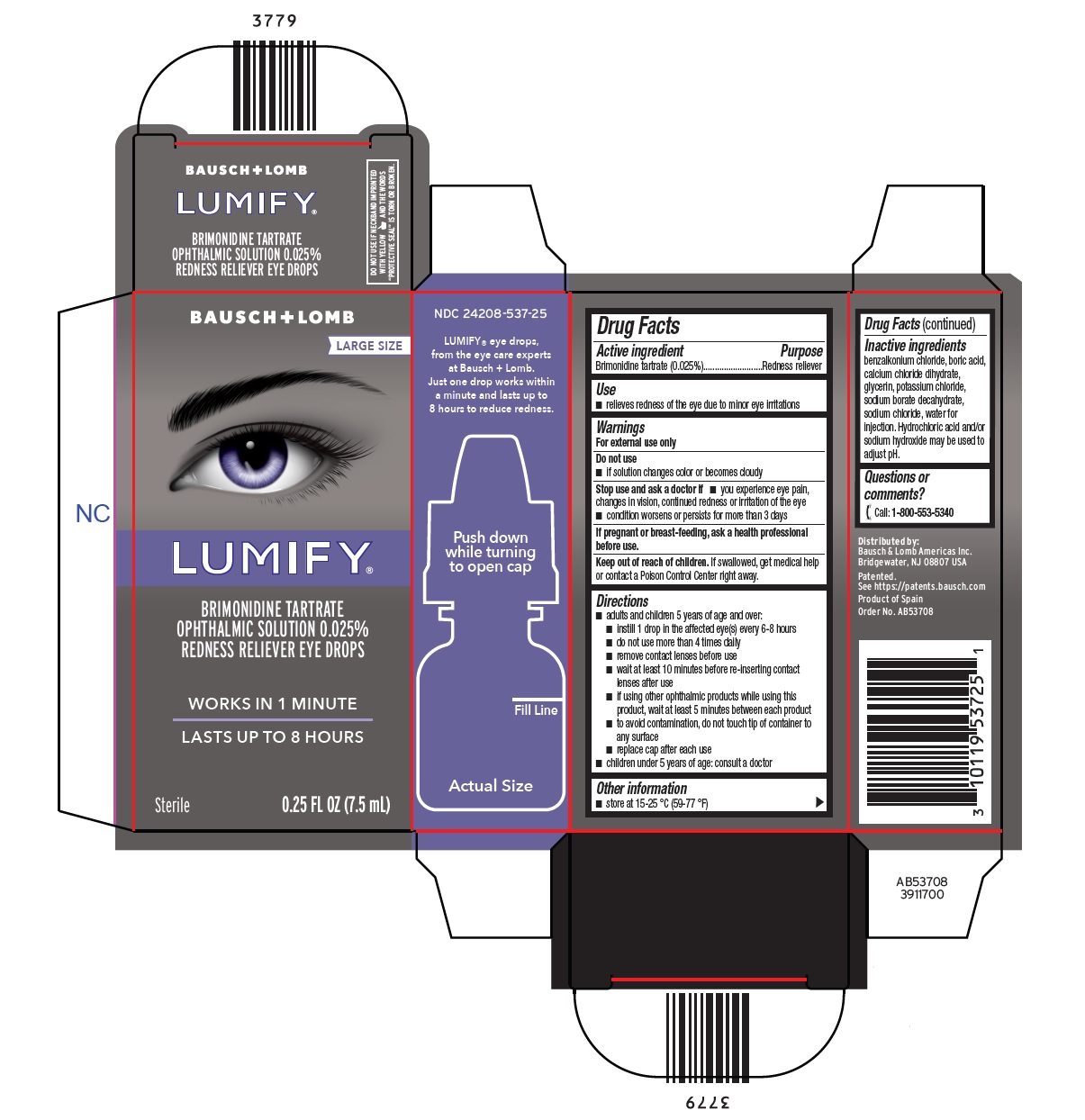 DRUG LABEL: LUMIFY Redness Reliever Eye Drops
NDC: 24208-537 | Form: SOLUTION/ DROPS
Manufacturer: Bausch & Lomb Incorporated
Category: otc | Type: HUMAN OTC DRUG LABEL
Date: 20250129

ACTIVE INGREDIENTS: BRIMONIDINE TARTRATE 0.25 mg/1 mL
INACTIVE INGREDIENTS: BENZALKONIUM CHLORIDE; BORIC ACID; CALCIUM CHLORIDE; GLYCERIN; POTASSIUM CHLORIDE; SODIUM BORATE; SODIUM CHLORIDE; WATER

Drug Facts

Active ingredient

Brimonidine tartrate (0.025%)

Purpose

Redness reliever

Use

- relieves redness of the eye due to minor eye irritations

Warnings

For external use only

Do not use

- if solution changes color or becomes cloudy

Stop use and ask a doctor if

- you experience eye pain, changes in vision, continued redness or irritation of the eye
- condition worsens or persists for more than 3 days

Keep out of reach of children.If swallowed, get medical help or contact a Poison Control Center right away.

Directions

- adults and children 5 years of age and over:
- instill 1 drop in the affected eye(s) every 6-8 hours
- do not use more than 4 times daily
- remove contact lenses before use
- wait at least 10 minutes before re-inserting contact lenses after use
- if using other ophthalmic products while using this product, wait at least 5 minutes between each product
- to avoid contamination, do not touch tip of container to any surface
- replace cap after each use
- children under 5 years of age: consult a doctor

Other information

- store at 15-25°C (59-77°F)

Inactive ingredients

benzalkonium chloride, boric acid, calcium chloride dihydrate, glycerin, potassium chloride, sodium borate decahydrate, sodium chloride, water for injection. Hydrochloric acid and/or sodium hydroxide may be used to adjust pH.

Questions or comments?

[phone icon] Call: 1-800-553-5340

PRINCIPAL DISPLAY PANEL - 7.5 mL Carton

BAUSCH + LOMB

LARGE SIZE

LUMIFY®

BRIMONIDINE TARTRATE
OPHTHALMIC SOLUTION 0.025%
REDNESS RELIEVER EYE DROPS

- WORKS IN 1 MINUTE
- LASTS UP TO 8 HOURS

Sterile 0.25 FL OZ (7.5 mL)

AB53708

3911700